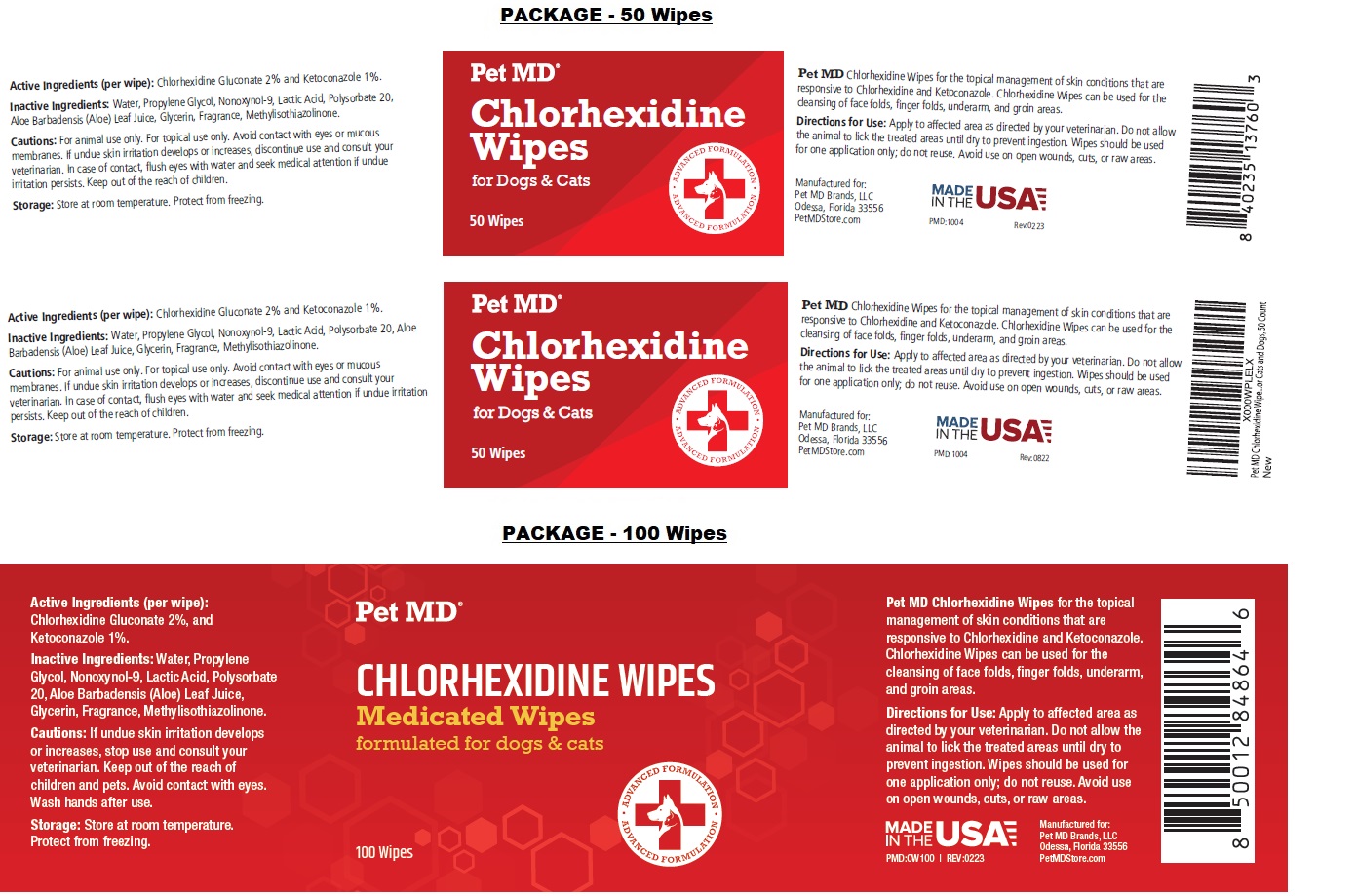 DRUG LABEL: Pet MD Chlorhexidine Wipes
NDC: 86090-011 | Form: CLOTH
Manufacturer: Pet MD Brands, LLC
Category: animal | Type: OTC ANIMAL DRUG LABEL
Date: 20230908

ACTIVE INGREDIENTS: CHLORHEXIDINE GLUCONATE 2 g/100 g; KETOCONAZOLE 1 g/100 g
INACTIVE INGREDIENTS: WATER; PROPYLENE GLYCOL; NONOXYNOL-9; LACTIC ACID, UNSPECIFIED FORM; POLYSORBATE 20; ALOE VERA LEAF; GLYCERIN; METHYLISOTHIAZOLINONE

Pet MD® Chlorhexidine Wipes

Active Ingredients (per wipe):

Chlorhexidine Gluconate 2% and Ketoconazole 1%.

INDICATIONS AND USAGE

Pet MD Chlorhexidine Wipes for the topical management of skin conditions that are responsive to Chlorhexidine and Ketoconazole. Chlorhexidine Wipes can be used for the cleansing of face folds, finger folds, underarm, and groin areas.

Inactive Ingredients:

Water, Propylene Glycol, Nonoxynol-9, Lactic Acid, Polysorbate 20, Aloe Barbadensis (Aloe) Leaf Juice, Glycerin, Fragrance, Methylisothiazolinone.

Cautions:

For animal use only. For topical use only. Avoid contact with eyes or mucous membranes. If undue skin irritation develops or increases, discontinue use and consult your veterinarian. In case of contact, flush eyes with water and seek medical attention if undue irritation persists. Keep out of the reach of children.

Storage:

Store at room temperature. Protect from freezing.

Directions for Use:

Apply to affected area as directed by your veterinarian. Do not allow the animal to lick the treated areas until dry to prevent ingestion. Wipes should be used for one application only; do not reuse. Avoid use on open wounds, cuts, or raw areas.

Medicated Wipes

formulated for dogs & cats

ADVANCED FORMULATION

Manufactured for:
Pet MD Brands, LLC
Odessa, Florida 33556
PetMDStore.com

MADE IN THE USA